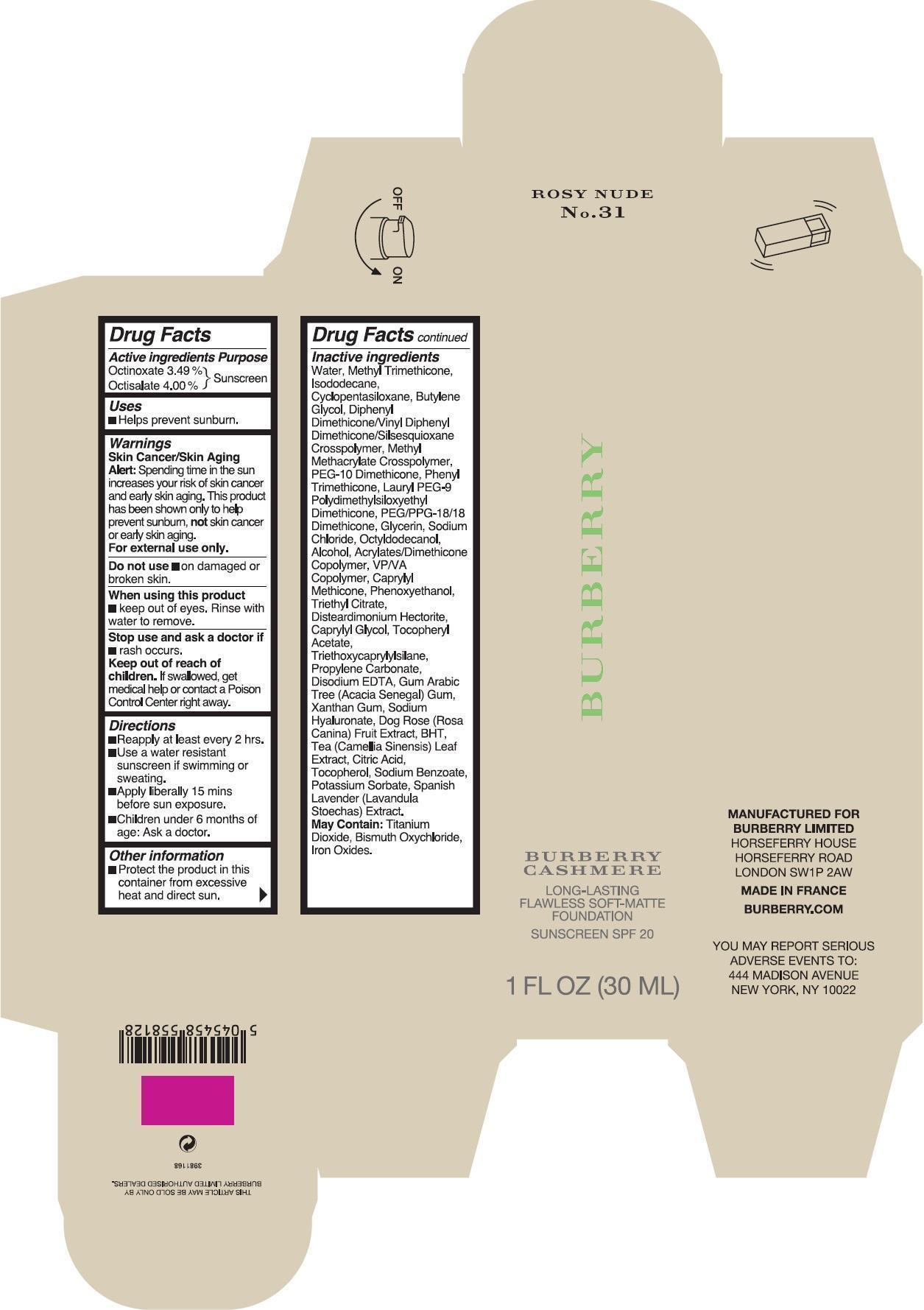 DRUG LABEL: Burberry Cashmere Long-Lasting Flawless Soft-Matte Foundation Sunscreen SPF20 Rosy Nude
NDC: 69038-044 | Form: CREAM
Manufacturer: Burberry Limited
Category: otc | Type: HUMAN OTC DRUG LABEL
Date: 20171225

ACTIVE INGREDIENTS: OCTINOXATE 34.9 mg/1 mL; OCTISALATE 40 mg/1 mL
INACTIVE INGREDIENTS: WATER; METHYL TRIMETHICONE; ISODODECANE; CYCLOMETHICONE 5; BUTYLENE GLYCOL; PHENYL TRIMETHICONE; LAURYL PEG-9 POLYDIMETHYLSILOXYETHYL DIMETHICONE; PEG/PPG-18/18 DIMETHICONE; GLYCERIN; SODIUM CHLORIDE; OCTYLDODECANOL; ALCOHOL; PVP/VA COPOLYMER; CAPRYLYL TRISILOXANE; PHENOXYETHANOL; TRIETHYL CITRATE; DISTEARDIMONIUM HECTORITE; CAPRYLYL GLYCOL; .ALPHA.-TOCOPHEROL ACETATE; TRIETHOXYCAPRYLYLSILANE; PROPYLENE CARBONATE; EDETATE DISODIUM; XANTHAN GUM; HYALURONATE SODIUM; BUTYLATED HYDROXYTOLUENE; TEA LEAF; CITRIC ACID MONOHYDRATE; TOCOPHEROL; SODIUM BENZOATE; POTASSIUM SORBATE; FERRIC OXIDE RED

Burberry Cashmere Long-Lasting Flawless Soft-Matte Foundation Sunscreen SPF20 Rosy Nude No. 31

Active ingredients

Octinoxate 3.49%

Octisalate 4.00%

Purpose

Sunscreen

Uses

- Helps Prevent Sunburn.

Warnings

Skin Cancer/Skin Aging Alert: Spending time in the sun increases your risk of skin cancer and early skin aging. This product has been shown only to help prevent sunburn, not skin cancer or early skin aging.

For external use only.

Do not use

- on damaged or broken skin.

When using this product

- keep out of eyes. Rinse with water to remove.

Stop use and ask a doctor if

rash occurs.

Keep out of reach of children.

If swallowed, get medical help or contact a Poison Control Center right away.

Directions

- Reapp ly at least every 2 hrs.
- Use a water resistant sunscreen if swimming or sweating.
- Apply liberal ly 15 mins before sun exposure.
- Children under 6 months of age: Ask a doctor.

Other information

Protect the product in this container from excessive heat and direct sun.

Inactive ingredients

Water, Methyl Trimethicone, Isododecane, Cyclopentasiloxane, Butylene Glycol, Diphenyl Dimethicone/Vinyl Diphenyl Dimethicone/Silsesquioxane Crosspolymer, Methyl Methacrylate Crosspolymer, PEG-10 Dimethicone, Phenyl Trimethicone, Lauryl PEG-9 Polydimethylsiloxyethyl Dimethicone, PEG/PPG-18/18 Dimethicone, Glycerin, Sodium Chloride, Octyldodecanol, Alcohol, Acrylates/Dimethicone Copolymer, VP/VA Copolymer, Caprylyl Methicone, Phenoxyethanol, Triethyl Citrate, Disteardimonium Hectorite, Caprylyl Glycol, Tocopheryl Acetate, Triethoxycaprylylsilane, Propylene Carbonate, Disodium EDTA, Gum Arabic Tree (Acacia Senegal) Gum, Xanthan Gum, Sodium Hyaluronate, Dog Rose (Rosa Canina) Fruit Extract, BHT, Tea (Camellia Sinensis) Leaf Extract, Citric Acid, Tocopherol, Sodium Benzoate, Potassium Sorbate, Spanish Lavender (Lavandula Stoechas) Extract. May Contain: Titanium Dioxide, Bismuth Oxychloride, Iron Oxides.